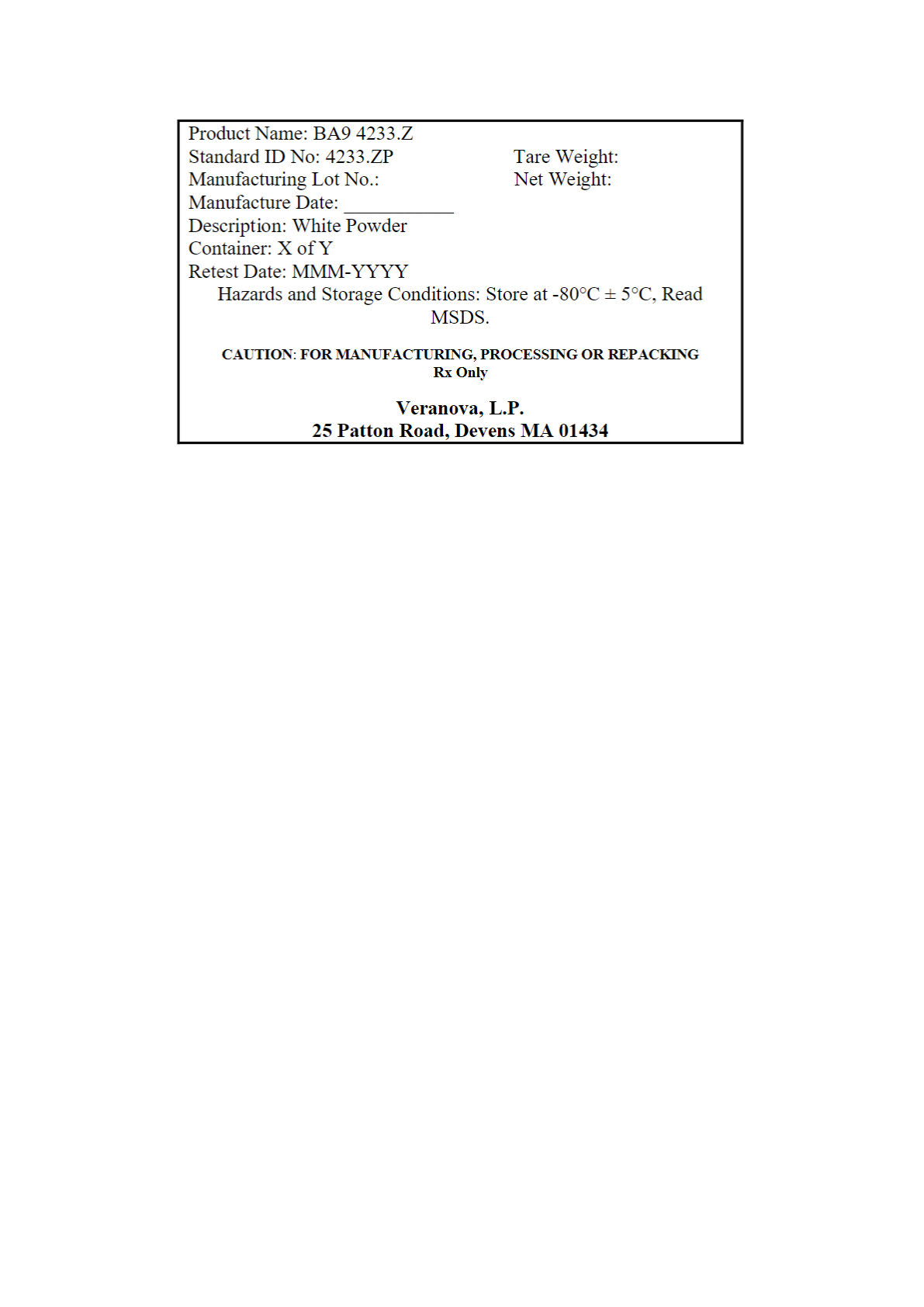 DRUG LABEL: BA9
NDC: 50137-4233 | Form: POWDER
Manufacturer: Veranova, L.P.
Category: other | Type: BULK INGREDIENT
Date: 20260106

ACTIVE INGREDIENTS: UMIROLIMUS 1 kg/1 kg

BA9 (4233.Z)